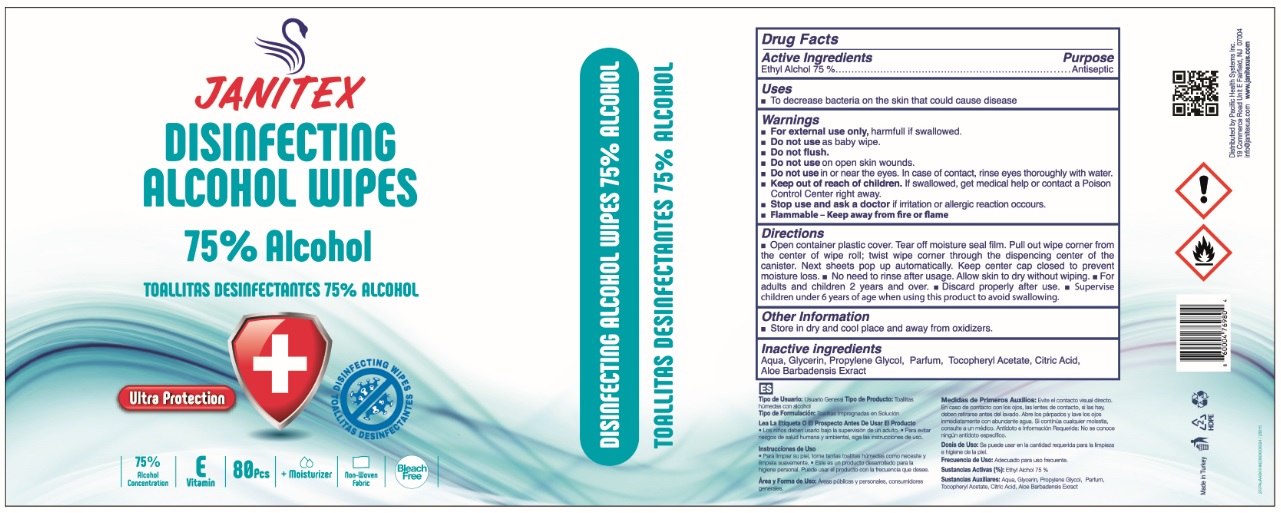 DRUG LABEL: JANITEX DISINFECTING WIPES 75% ALCOHOL
NDC: 79519-060 | Form: CLOTH
Manufacturer: Pacific Health Systems Inc.
Category: otc | Type: HUMAN OTC DRUG LABEL
Date: 20200811

ACTIVE INGREDIENTS: ALCOHOL 75 g/100 g
INACTIVE INGREDIENTS: WATER; GLYCERIN; PROPYLENE GLYCOL; .ALPHA.-TOCOPHEROL ACETATE; CITRIC ACID MONOHYDRATE; ALOE VERA LEAF

JANITEX DISINFECTING ALCOHOL WIPES

Active Ingredients

Ethyl Alcohol 75 %

Purpose

Antiseptic

Uses

- To decrease bacteria on the skin that could cause disease

Warnings

- For external use only, harmful if swallowed.
- Do not use as baby wipe.
- Do not flush.
- Do not use on open skin wounds.
- Do not use in or near the eyes. In case of contact, rinse eyes thoroughly with water.
- Stop use and ask a doctor if irritation or allergic reaction occurs.
- Flammable - Keep away from fire or flame

• Keep out of reach of children. If swallowed, get medical help or contact a Poison Control Center right away.

Directions

• Open container plastic cover. Tear off moisture seal film. Pull out wipe corner from the center of wipe roll; twist wipe corner through the dispensing center of the canister. Next sheets pop up automatically. Keep center cap closed to prevent moisture loss. • No need to rinse after usage. Allow skin to dry without wiping. For adults and children 2 years and over. • Discard properly after use. • Supervise children under 6 years of age when using this product to avoid swallowing.

Other Information

- Store in dry and cool place and away from oxidizers.

Inactive ingredients

Aqua, Glycerin, Propylene Glycol, Parfum, Tocopheryl Acetate, Citric Acid, Aloe Barbadensis Extract

75% Alcohol

75% Alcohol Concentration

E Vitamin

+ moisturizer

non-woven fabric

Bleach Free

Ultra Protection

DISINFECTING WIPES

Distributed by Pacific Health Systems Inc.

19 Commerce Road Unit E Fairfield, NJ 07004

info@janitexus.com www.janitexus.com

Made in Turkey